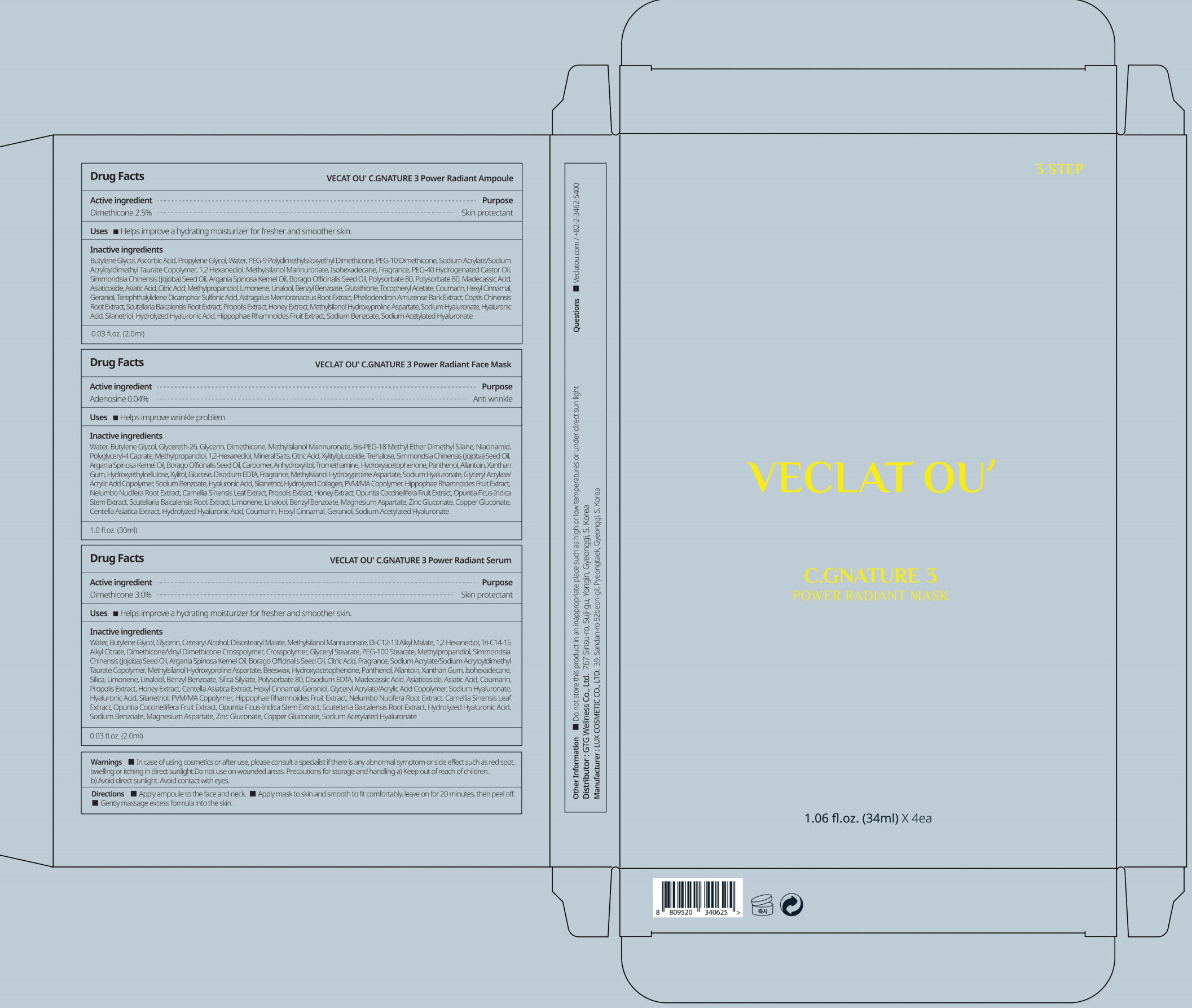 DRUG LABEL: VECLAT OU C.GNATURE 3 Power Radiant Serum
NDC: 71080-0028 | Form: LIQUID
Manufacturer: GTG WELLNESS CO., LTD.
Category: otc | Type: HUMAN OTC DRUG LABEL
Date: 20211124

ACTIVE INGREDIENTS: Dimethicone 3.0 g/100 mL
INACTIVE INGREDIENTS: Water; Butylene Glycol; Glycerin; Diisostearyl Malate

ACTIVE INGREDIENT

Dimethicone 3.0%

INACTIVE INGREDIENTS

Water, Butylene Glycol, Glycerin, Cetearyl Alcohol, Diisostearyl Malate, Methylsilanol Mannuronate, Di-C12-13 Alkyl Malate, 1,2 Hexanediol, Tri-C14-15 Alkyl Citrate, Dimethicone/Vinyl Dimethicone Crosspolymer, Crosspolymer, Glyceryl Stearate, PEG-100 Stearate, Methylpropandiol, Simmondsia Chinensis (Jojoba) Seed Oil, Argania Spinosa Kernel Oil, Borago Officinalis Seed Oil, Citric Acid, Fragrance, Sodium Acrylate/Sodium
Acryloyldimethyl Taurate Copolymer, Methylsilanol Hydroxyproline Aspartate, Beeswax, Hydroxyacetophenone, Panthenol, Allantoin, Xanthan Gum, Isohexadecane, Silica, Limonene, Linalool, Benzyl Benzoate, Silica Silylate, Polysorbate 80, Disodium EDTA, Madecassic Acid, Asiaticoside, Asiatic Acid, Coumarin, Propolis Extract, Honey Extract, Centella Asiatica Extract, Hexyl Cinnamal, Geraniol, Glyceryl Acrylate/Acrylic Acid Copolymer, Sodium Hyaluronate, Hyaluronic Acid, Silanetriol, PVM/MA Copolymer, Hippophae Rhamnoides Fruit Extract, Nelumbo Nucifera Root Extract, Camellia Sinensis Leaf Extract, Opuntia Coccinellifera Fruit Extract, Opuntia Ficus-Indica Stem Extract, Scutellaria Baicalensis Root Extract, Hydrolyzed Hyaluronic Acid, Sodium Benzoate, Magnesium Aspartate, Zinc Gluconate, Copper Gluconate, Sodium Acetylated Hyaluronate

PURPOSE

Skin protectant

WARNINGS

In case of using cosmetics or after use, please consult a specialist if there is any abnormal symptom or side effect such as red spot, swelling or itching in direct sunlight.
Do not use on wounded areas.
Precautions for storage and handling
a) Keep out of reach of children.
b) Avoid direct sunlight.
Avoid contact with eyes.

KEEP OUT OF REACH OF CHILDREN

Uses

■ Helps improve a hydrating moisturizer for fresher and smoother skin.

Directions

■ Apply ampoule to the face and neck.
■ Apply mask to skin and smooth to fit comfortably, leave on for 20 minutes, then peel off.
■ Apply serum to the entire face and neck.

Other information

■ Do not store this product in an inappropriate place such as high or low temperatures or under direct sun light

Questions

■ Veclatou.com / +82-2-3462-5400